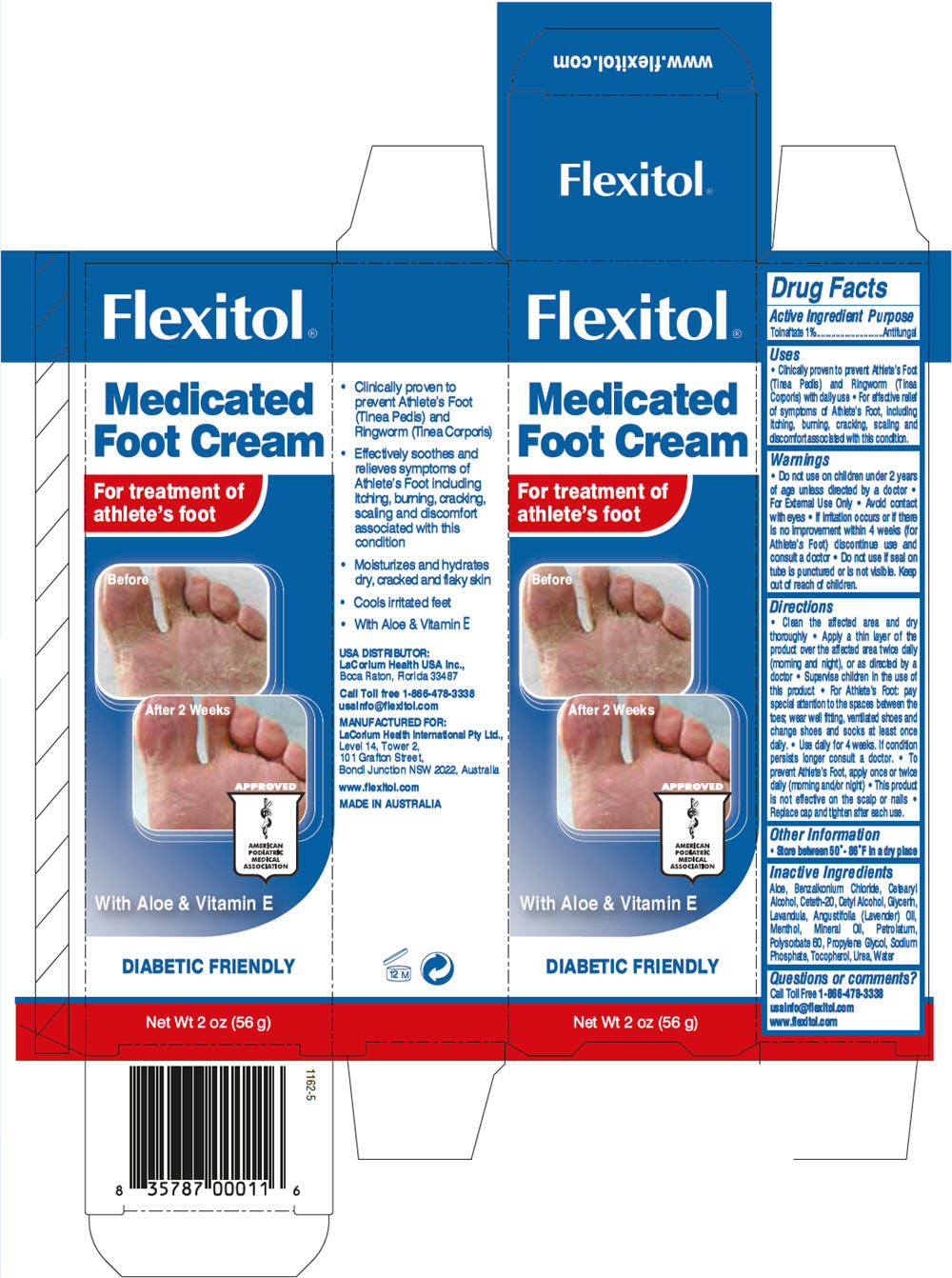 DRUG LABEL: Flexitol Medicated Foot
NDC: 43251-3340 | Form: CREAM
Manufacturer: LaCorium Health International Pty Ltd
Category: otc | Type: HUMAN OTC DRUG LABEL
Date: 20121112

ACTIVE INGREDIENTS: Tolnaftate 1 g/100 g
INACTIVE INGREDIENTS: Urea; Cetostearyl Alcohol; Mineral Oil; Glycerin; Propylene glycol; Petrolatum; Polysorbate 60; Ceteth-20; Cetyl alcohol; Menthol; Sodium phosphate; Benzalkonium chloride; Tocopherol; Lavender Oil; Aloe Vera Leaf; Water

Flexitol Medicated Foot Cream

Drug Facts

Active Ingredient

Tolnaftate 1%

Purpose

Antifungal

Uses

- Clinically proven to prevent Athlete's Foot (Tinea Pedis) and Ringworm (Tinea Corporis) with daily use
- For effective relief of symptoms of Athlete's Foot, including itching, burning, cracking, scaling and discomfort associated with this condition.

Warnings

- Do not use on children under 2 years of age unless directed by a doctor

WHEN USING

- For External Use Only
- Avoid contact with eyes

STOP USE

- If irritation occurs or if there is no improvement within 4 weeks (for Athlete's Foot) discontinue use and consult a doctor

- Do not use if seal on tube is punctured or is not visible. Keep out of reach of children.

Directions

- Clean the affected area and dry thoroughly
- Apply a thin layer of the product over the affected area twice daily (morning and night), or as directed by a doctor
- Supervise children in the use of this product
- For Athlete's Foot: pay special attention to the spaces between the toes; wear well fitting, ventilated shoes and change shoes and socks at least once daily.
- Use daily for 4 weeks. If condition persists longer consult a doctor.
- To prevent Athlete's Foot, apply once or twice daily (morning and/or night)
- This product is not effective on the scalp or nails
- Replace cap and tighten after each use.

Other Information

- Store between 50°- 86°F in a dry place

Inactive Ingredients

Aloe, Benzalkonium Chloride, Cetearyl Alcohol, Ceteth-20, Cetyl Alcohol, Glycerin, Lavandula, Angustifolia (Lavender) Oil, Menthol, Mineral Oil, Petrolatum, Polysorbate 60, Propylene Glycol, Sodium Phosphate, Tocopherol, Urea, Water

Questions or comments?

Call Toll Free 1-866-478-3338
usainfo@flexitol.com
www.flexitol.com

USA DISTRIBUTOR:
LaCorium Health USA Inc.,
Boca Raton, Florida 33487

MANUFACTURED FOR:
LaCorium Health International Pty Ltd.,
Level 14, Tower 2,
101 Grafton Street,
Bondi Junction NSW 2022, Australia

PRINCIPAL DISPLAY PANEL - 56 g Tube Carton

Flexitol®

Medicated
Foot Cream

For treatment of
athlete's foot

Before

After 2 Weeks

APPROVED

AMERICAN
PODIATRIC
MEDICAL
ASSOCIATION

With Aloe & Vitamin E

DIABETIC FRIENDLY

Net Wt 2 oz (56 g)